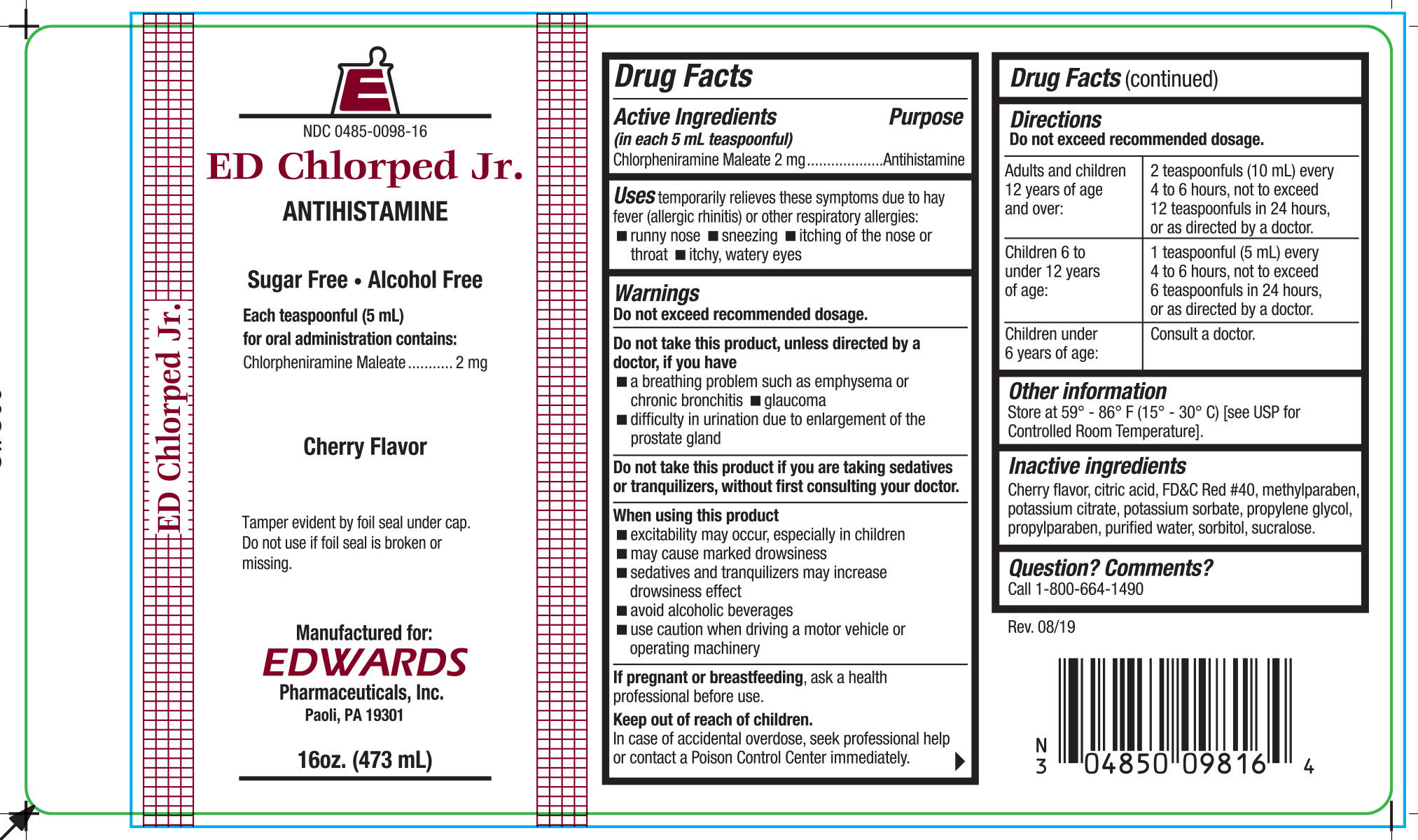 DRUG LABEL: ED CHLORPED JR
NDC: 0485-0098 | Form: LIQUID
Manufacturer: EDWARDS PHARMACEUTICALS, INC.
Category: otc | Type: HUMAN OTC DRUG LABEL
Date: 20251028

ACTIVE INGREDIENTS: CHLORPHENIRAMINE MALEATE 2 mg/5 mL
INACTIVE INGREDIENTS: CITRIC ACID MONOHYDRATE; FD&C RED NO. 40; METHYLPARABEN; POTASSIUM CITRATE; POTASSIUM SORBATE; PROPYLPARABEN; PROPYLENE GLYCOL; WATER; SORBITOL; SUCRALOSE

ED CHLORPED JR.

Drug Facts

Active Ingredients (in each 5 mL teaspoonful)

Chlorpheniramine Maleate 2 mg

Purpose

Antihistamine

Uses

temporarily relieves these symptoms due to hay fever (allergic rhinitis) or other respiratory allergies:

- runny nose
- sneezing
- itching of the nose or throat
- itchy, watery eyes

Warnings

Do not exceed recommended dosage.

Do not take this product, unless directed by a doctor, if you have

- a breathing problem such as emphysema or chronic bronchitis
- glaucoma
- difficulty in urination due to enlargement of the prostate gland

ASK DOCTOR

Do not take this product if you are taking sedatives or tranquilizers, without first consulting your doctor.

When using this product

- excitability may occur, especially in children
- may cause marked drowsiness
- sedatives and tranquilizers may increase drowsiness effect
- avoid alcoholic beverages
- use caution when driving a motor vehicle or operating machinery

PREGNANCY OR BREAST FEEDING

If pregnant or breastfeeding, ask a health professional before use.

Keep out of reach of children.

In case of accidental overdose, seek professional help or contact a Poison Control Center immediately.

Directions

Do not exceed recommended dosage.

Adults and children 12 years of age and over: | 2 teaspoonfuls (10 mL) every 4 to 6 hours, not to exceed 12 teaspoonfuls in 24 hours, or as directed by a doctor.
Children 6 to under 12 years of age: | 1 teaspoonful (5 mL) every 4 to 6 hours, not to exceed 6 teaspoonfuls in 24 hours, or as directed by a doctor.
Children under 6 years of age: | Consult a doctor
 | .

Other information

Store at 59° - 86° F (15° - 30° C) [see USP for Controlled Room Temperature].

Inactive ingredients

Cherry Flavor, Citric Acid, FD&C Red # 40, Methyl Paraben, Potassium Citrate, Potassium Sorbate, Propyl Paraben, Propylene Glycol, Purified Water, Sorbitol Solution 70%, Sucralose.

Question? Comments?

Call 1-800-543-9560

PRINCIPAL DISPLAY PANEL - 473 mL Bottle Label

NDC 0485-0098-16

ED Chlorped Jr.

ANTIHISTAMINE

FOR PROFESSIONAL USE ONLY

Sugar Free • Alcohol Free

Each teaspoonful (5 mL)
for oral administration contains:
Chlorpheniramine Maleate 2 mg

Cherry Flavor

Tamper evident by foil seal under cap.
Do not use if foil seal is broken or missing.

Manufactured for:
EDWARDS Pharmaceuticals, Inc.
Paoli, PA 19301

16oz. (473 mL)